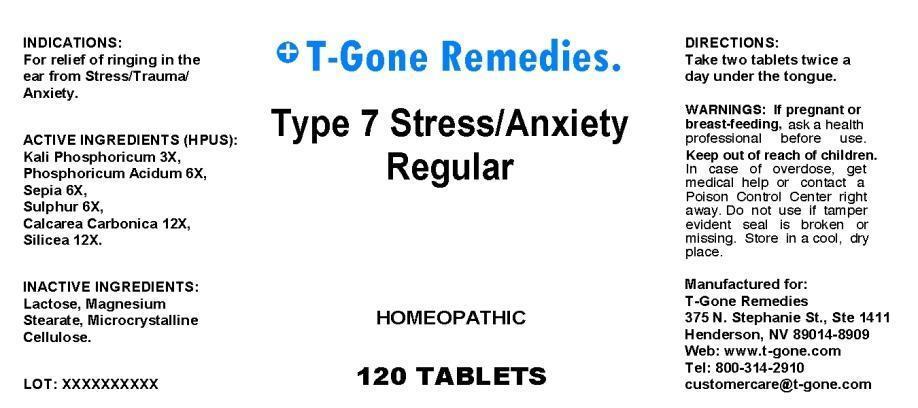 DRUG LABEL: Type 7 Stress Anxiety Regular
NDC: 50169-0004 | Form: TABLET, ORALLY DISINTEGRATING
Manufacturer: T-Gone Remedies
Category: homeopathic | Type: HUMAN OTC DRUG LABEL
Date: 20130424

ACTIVE INGREDIENTS: POTASSIUM PHOSPHATE, DIBASIC 3 [hp_X]/1 mg; PHOSPHORIC ACID 6 [hp_X]/1 mg; SEPIA OFFICINALIS JUICE 6 [hp_X]/1 mg; SULFUR 6 [hp_X]/1 mg; OYSTER SHELL CALCIUM CARBONATE, CRUDE 12 [hp_X]/1 mg; SILICON DIOXIDE 12 [hp_X]/1 mg
INACTIVE INGREDIENTS: LACTOSE; MAGNESIUM STEARATE; CELLULOSE, MICROCRYSTALLINE

Drug Facts

ACTIVE INGREDIENTS

Kali Phosphoricum 3X, Phosphoricum Acidum 6X, Sepia 6X, Sulphur 6X, Calcarea Carbonica 12X, Silicea 12X

INDICATIONS

For relief of ringing in the ear from Stress, Trauma, Anxiety.

WARNINGS

If pregnant or breast-feeding, ask a health professional before use. Keep out of reach of children. In case of overdose, get medical help or contact a Poison Control Center right away. Do not use if tamper evident seal is broken or missing. Store in a cool, dry place.

DIRECTIONS

Take tablets twice a day under the tongue.

INACTIVE INGREDIENTS

Lactose, Magnesium Stearate, Microcrystalline Cellulose

KEEP OUT OF REACH OF CHILDREN

In case of overdose, get medical help or contact a Poison Control Center right away.

INDICATIONS AND USAGE

For relief of ringing in the ear from Stress, Trauma, Anxiety.

QUESTIONS

Manufactured for:

T-Gone Remedies

375 N. Stephanie St., Ste. 1411

Henderson, NV 89014-8909

Web: www.t-gone.com

Tel: 800-314-2910

PACKAGE LABEL

T-Gone Remedies

Type 7 Stress Anxiety

Regular

HOMEOPATHIC

120 TABLETS